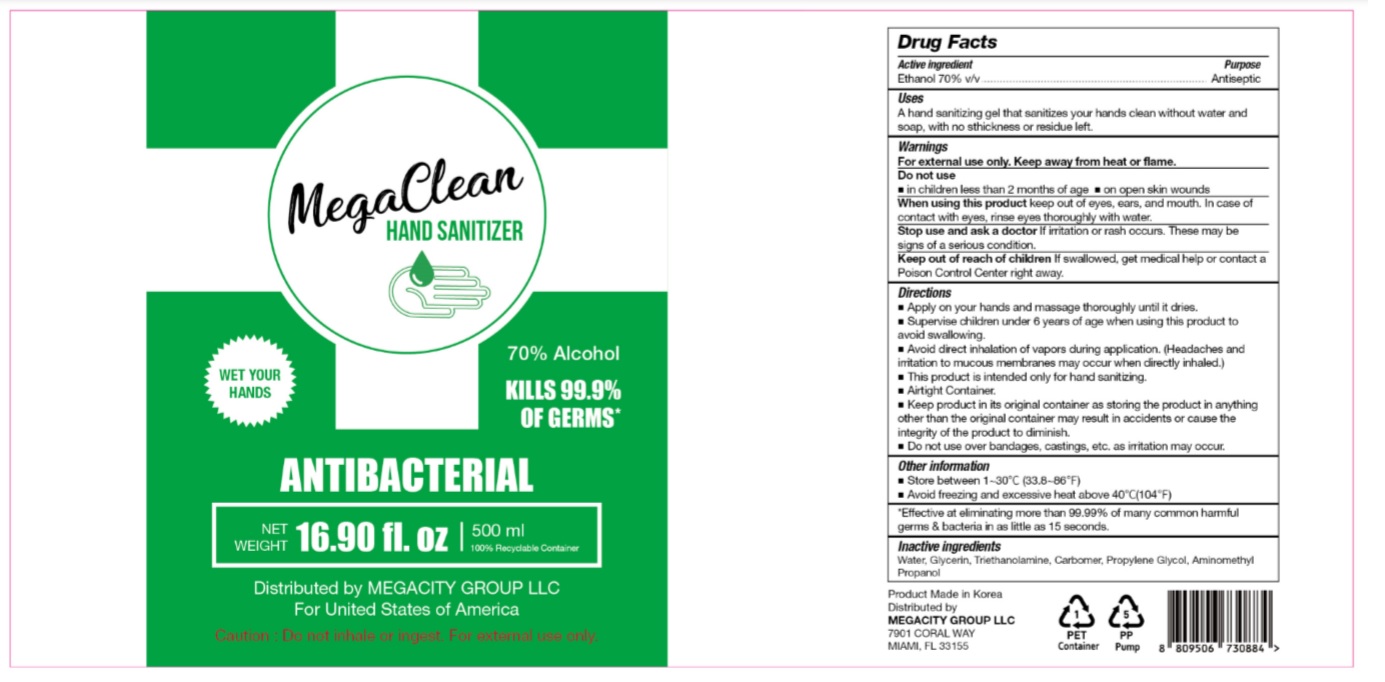 DRUG LABEL: MegaClean HAND SANITIZER
NDC: 77799-570 | Form: GEL
Manufacturer: MEGACITY GROUP LLC
Category: otc | Type: HUMAN OTC DRUG LABEL
Date: 20200527

ACTIVE INGREDIENTS: ALCOHOL 350 mL/500 mL
INACTIVE INGREDIENTS: AMINOMETHYLPROPANOL; GLYCERIN; WATER; PROPYLENE GLYCOL; TROLAMINE; CARBOMER HOMOPOLYMER, UNSPECIFIED TYPE

MegaClean HAND SANITIZER 500 mL
77799-570-01